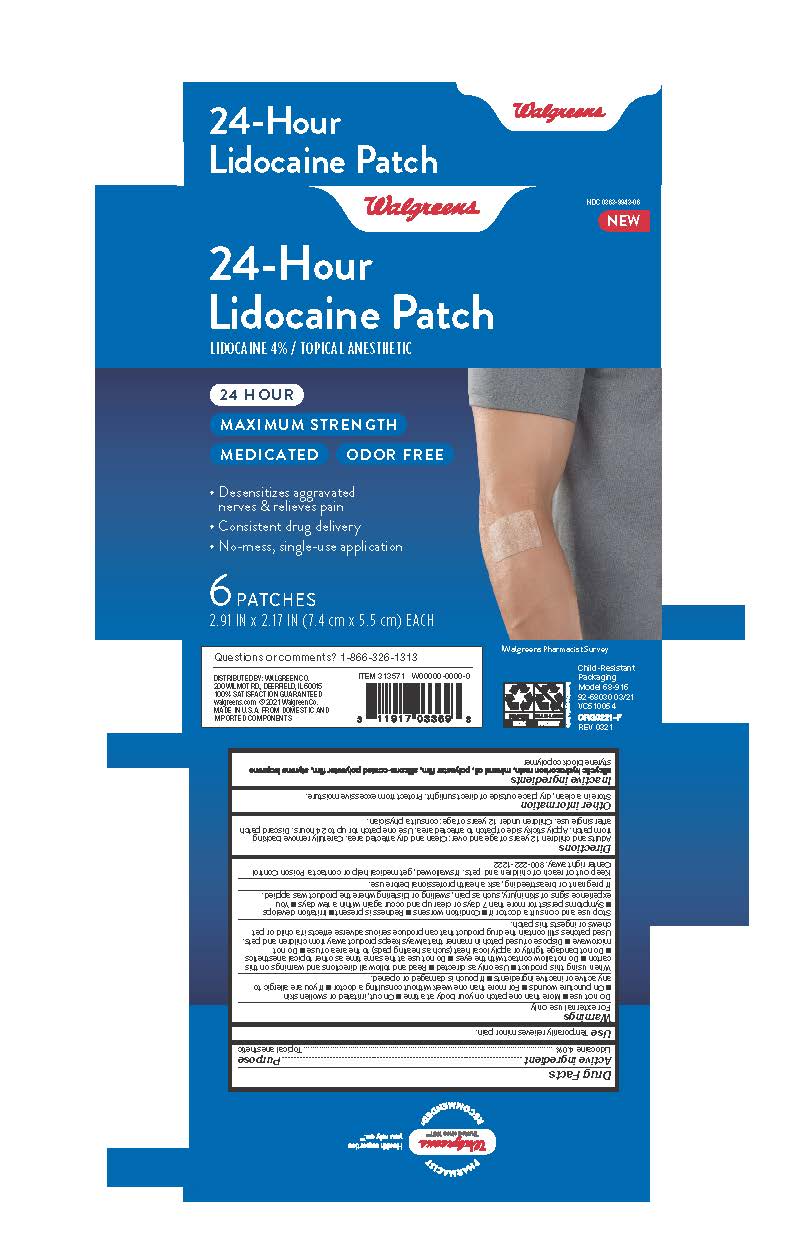 DRUG LABEL: Walgreens 24-Hour Lidocaine Patch
NDC: 0363-9943 | Form: PATCH
Manufacturer: Walgreens Company
Category: otc | Type: HUMAN OTC DRUG LABEL
Date: 20251227

ACTIVE INGREDIENTS: LIDOCAINE 4 g/100 g
INACTIVE INGREDIENTS: HYDROGENATED C6-20 POLYOLEFIN (100 CST); MINERAL OIL; STYRENE/ISOPRENE/STYRENE BLOCK COPOLYMER

Walgreens 24 Hour Lidocaine Patch

Active Ingredient

Lidocaine 4.0%

Purpose

Topical Anesthetic

Use

Temporarily relieves minor pain

Warnings

For External Use Only

Do not Use

- More than one patch on your body at a time
- On cut, irritated or swollen skin
- On puncture wounds
- For more than one week without consulting a doctor
- If you are allergic to any active or inactive ingredients
- If pouch is damaged or opened.

When using this product

- Use only as directed
- Read and follow all directions and warnings on this carton
- Do not allow contact with the eyes
- Do not use at the same time as other topical anesthetics
- Do not bandage tightly or apply local heat (such as heating pads) to the area of use
- Do not microwave
- Dispose of used patch in manner that always keeps product away from children and pets. Used patches still contain the drug product that can produce serious adverse effects is a child or pet chews or ingests this patch.

Stop use and consult a doctor if

- Condition worsen
- Redness is present
- Irritation develops
- Symptoms persist for more than 7 days or clear up and occur again within a few days
- You experience signs of skin injury, such as pain, swelling, or blistering where the product was applied.

Keep out of reach of children and pets

If swallowed, get medical help or contact a Poison Control Center right away 800-222-1222

If pregnant or breastfeeding

ask a health professional before use

Directions

Adults and children 12 years of age and over: Clean and dry affected area. Carefully remove backing from patch. Apply sticky side of patch to affected area. Use one patch for up to 24 hours. Discard patch after single use. Children under 12 years of age: consult a physician.

Other Information

Store in a clean, dry place outside of direct sunlight. Protect from excessive moisture

Inactive Ingredients

alicyclic hydrocorbon resin, mineral oil, polyester film, silicone-coated polyester film, styrene isoprene styrene block copolymer